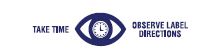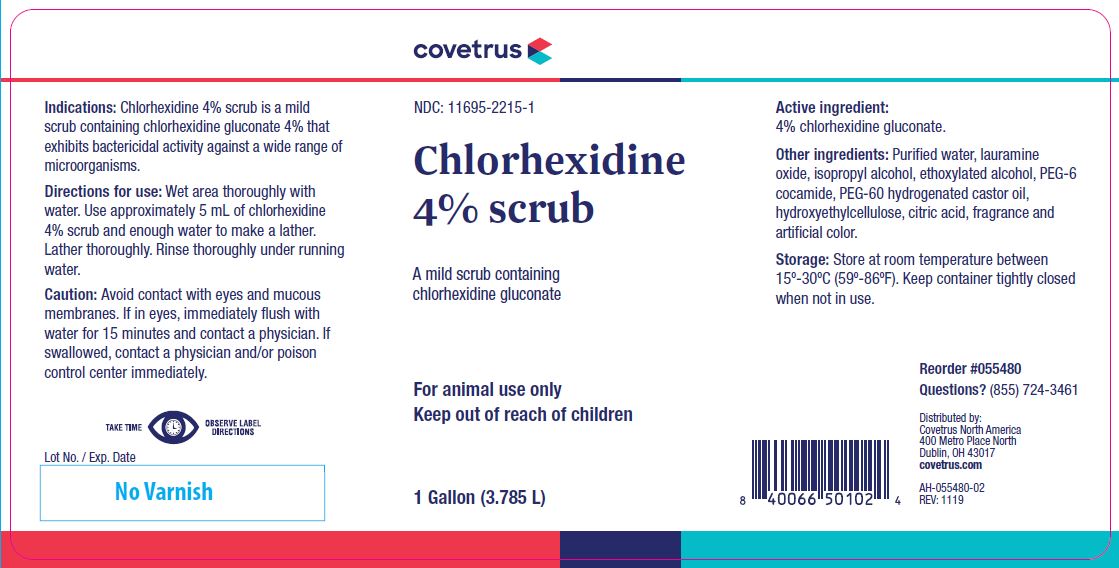 DRUG LABEL: Chlorhexidine
NDC: 11695-2215 | Form: LIQUID
Manufacturer: Butler Animal Health Supply, LLC dba Covetrus North America
Category: animal | Type: OTC ANIMAL DRUG LABEL
Date: 20221110

ACTIVE INGREDIENTS: CHLORHEXIDINE GLUCONATE 214.5 g/1 L

Chlorhexidine 4% scrub

STATEMENT OF IDENTITY

A mild scrub containing chlorhexidine gluconate

KEEP OUT OF REACH OF CHILDREN

For animal use only
Keep out of reach of children

HOW SUPPLIED

1 Gallon (3.785 L)

Indications:

Chlorhexidine 4% scrub is a mild scrub containing chlorhexidine gluconate 4% that exhibits bactericidal activity against a wide range of microorganisms.

Directions for use:

Wet area thoroughly with water. Use approximately 5 mL of chlorhexidine 4% scrub and enough water to make a lather.
Lather thoroughly. Rinse thoroughly under running water.

Caution:

Avoid contact with eyes and mucous membranes. If in eyes, immediately flush with water for 15 minutes and contact a physician. If swallowed, contact a physician and/or poison control center immediately.

Active ingredient:

4% chlorhexidine gluconate.

Other ingredients:

Purified water, lauramine oxide, isopropyl alcohol, ethoxylated alcohol, PEG-6 cocamide, PEG-60 hydrogenated castor oil, hydroxyethylcellulose, citric acid, fragrance and artificial color.

Storage:

Store at room temperature between 15º-30ºC (59º-86ºF). Keep container tightly closed when not in use.

INFORMATION FOR OWNERS/CAREGIVERS

Reorder #055480
Questions? (855) 724-3461
Distributed by:
Covetrus North America
400 Metro Place North
Dublin, OH 43017
covetrus.com

AH-055480-02
REV: 1119